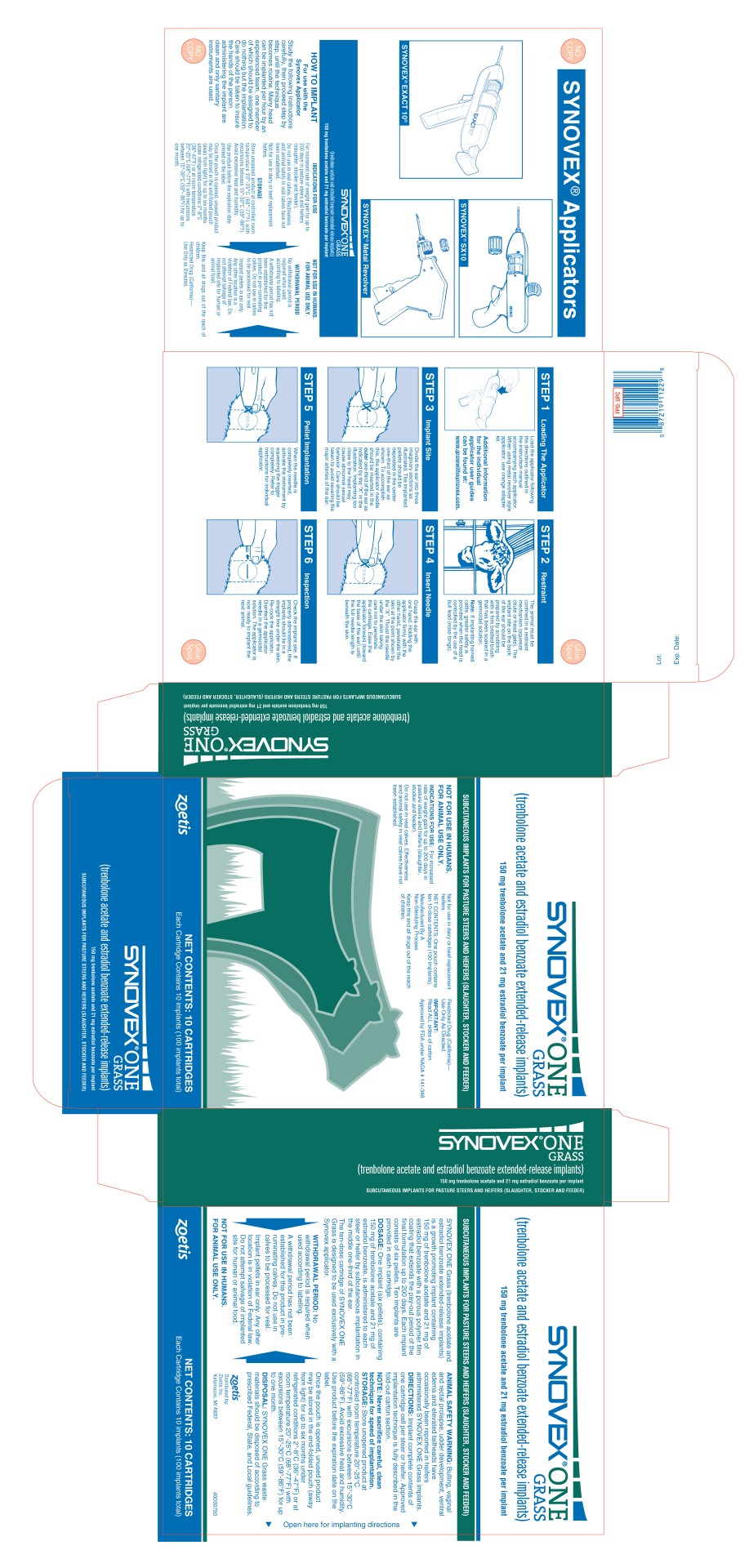 DRUG LABEL: Synovex One
NDC: 54771-2011 | Form: IMPLANT
Manufacturer: Zoetis Inc.
Category: animal | Type: OTC ANIMAL DRUG LABEL
Date: 20201026

ACTIVE INGREDIENTS: TRENBOLONE ACETATE 150 mg/1 1; ESTRADIOL BENZOATE 21 mg/1 1

SYNOVEX® ONE GRASS

SYNOVEX® ONE GRASS
(trenbolone acetate and estradiol benzoate extended-release implants)
150 mg trenbolone acetate and 21 mg estradiol benzoate per implant

SUBCUTANEOUS IMPLANTS FOR PASTURE STEERS AND HEIFERS (SLAUGHTER, STOCKER AND FEEDER)

Description

SYNOVEX ONE Grass (trenbolone acetate and estradiol benzoate extended-release implants) is a growth promoting implant containing 150 mg of trenbolone acetate and 21 mg of estradiol benzoate with a porous polymer film coating that extends the pay-out period of the final formulation up to 200 days. Each implant consists of 6 pellets. Ten implants are provided in each cartridge.

DOSAGE

One implant (six pellets), containing 150 mg of trenbolone acetate and 21 mg of estradiol benzoate, is administered to each steer or heifer by subcutaneous implantation in the middle one‑third of the ear.
The ten-dose cartridge of SYNOVEX ONE Grass is designed to be used exclusively with a Synovex Applicator.

WITHDRAWAL PERIOD

No withdrawal period is required when used according to labeling.

A withdrawal period has not been established for this product in pre-ruminating calves. Do not use in calves to be processed for veal.

Implant pellets in ear only. Any other location is a violation of Federal law. Do not attempt salvage of implanted site for human or animal food.

Warnings

NOT FOR USE IN HUMANS.

FOR ANIMAL USE ONLY.

ANIMAL SAFETY WARNING

Bulling, vaginal and rectal prolapse, udder development, ventral edema and elevated tailheads have occasionally been reported in heifers administered SYNOVEX ONE Grass implants.

DIRECTIONS

Implant complete contents of one cartridge cell per steer or heifer. Approved implantation technique is fully described in the fold-out carton section.

NOTE: Never sacrifice careful, clean technique for speed of implantation.

STORAGE

Store unopened product at controlled room temperature 20°-25°C (68°-77°F) with excursions between 15°-30°C (59°-86°F). Avoid excessive heat and humidity. Use product before the expiration date on the label.

Once the pouch is opened, unused product may be stored in the end-folded pouch (away from light) for up to six months under refrigerated conditions 2°-8°C (36°-47°F) or at room temperature 20°-25°C (68°-77°F) with excursions between 15°-30°C (59°-86°F) for up to one month.

DISPOSAL

SYNOVEX ONE Grass waste materials should be disposed of according to prescribed Federal, State, and Local guidelines.

INDICATIONS FOR USE

For increased rate of weight gain for up to 200 days in pasture steers and heifers (slaughter, stocker and feeder).

Do not use in veal calves. Effectiveness and animal safety in veal calves have not been established.

Not for use in dairy or beef replacement heifers.

NET CONTENTS

One pouch contains ten 10-dose cartridges (100 implants).

IMPORTANT: Read ALL sides of carton
Approved by FDA under NADA 141-348
zoetis
Distributed by:
Zoetis Inc.
Kalamazoo, MI 49007
6203A
40030750

PRINCIPAL DISPLAY PANEL - 10 Cartridge Implant Carton

SYNOVEX® ONE
GRASS
(trenbolone acetate and estradiol benzoate extended-release implants)
150 mg trenbolone acetate and 21 mg estradiol benzoate per implant

SUBCUTANEOUS IMPLANTS FOR PASTURE STEERS AND HEIFERS (SLAUGHTER, STOCKER AND FEEDER)

NOT FOR USE IN HUMANS.
FOR ANIMAL USE ONLY.

INDICATIONS FOR USE: For increased
rate of weight gain for up to 200 days in
pasture steers and heifers (slaughter,
stocker and feeder).

Do not use in veal calves. Effectiveness
and animal safety in veal calves have not
been established.

Not for use in dairy or beef replacement
heifers.

NET CONTENTS: One pouch contains
ten 10-dose cartridges (100 implants).

Manufactured By A
Non-Sterilizing Process

Keep this and all drugs out of the reach
of children.

Restricted Drug (California)—
Use Only As Directed.

IMPORTANT:
Read ALL sides of carton

Approved by FDA under NADA 141-348

zoetis

NET CONTENTS: 10 CARTRIDGES
Each Cartridge Contains 10 implants (100 implants total)